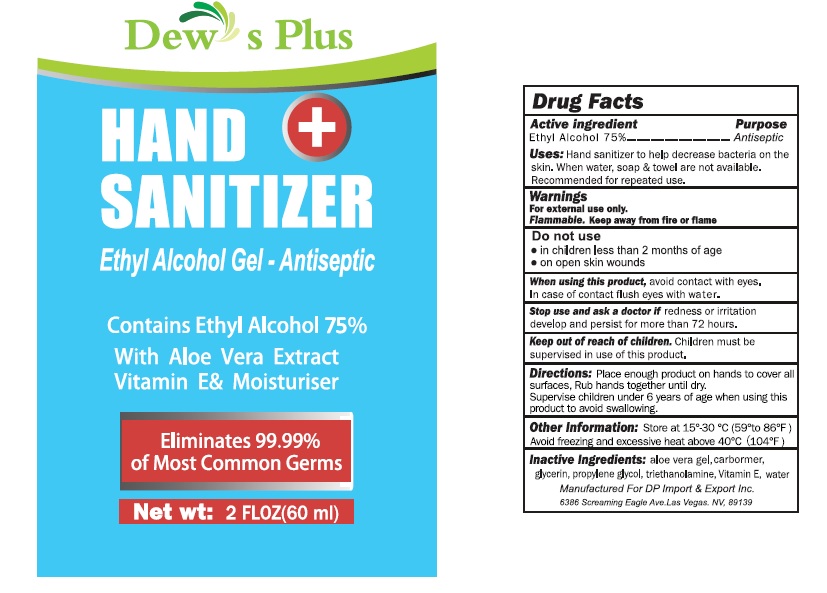 DRUG LABEL: Dews Plus
NDC: 73824-001 | Form: GEL
Manufacturer: DP IMPORT & EXPORT, INC.
Category: otc | Type: HUMAN OTC DRUG LABEL
Date: 20200413

ACTIVE INGREDIENTS: ALCOHOL 75 mL/100 mL
INACTIVE INGREDIENTS: WATER; GLYCERIN; ISOPROPYL ALCOHOL; CAPRYLYL GLYCOL; ISOPROPYL MYRISTATE; .ALPHA.-TOCOPHEROL ACETATE, D-; CARBOMER INTERPOLYMER TYPE A (ALLYL SUCROSE CROSSLINKED)

Dews Plus

Active Ingredient

Ethyl Alcohol

Purpose

Antiseptic

Uses

- Hand sanitizer to help decrease bacteria on the skin.
- When water, soap towel are not available
- Recommended for repeated use.

Warnings

External use only.

Flammable, Keep away from fire or flame

Do not use

- In children less than 2 months of age
- On open skin wounds

When using this product, avoid contact with eyes
in case of contact flush eyes with water.

Stop use and ask a doctor if redness or irritation
develop and persist for more than 72hours.

Keep out of reach of children.

Children must be supervised in use of this product.

Supervise children under 6 years of age when using this
product to avoid swallowing.

Directions

Place enough product on hands to cover all surfaces, Rub hands together until dry

Other Informatin

Store at15°30°c(59"to86F)
Avoid freezing and excessive heat above 40C(104%F)

Inactive Ingredient

water, triethanolamine
glycerin, propylene glycol, Vitamin E, aloe vera gel
carbomer